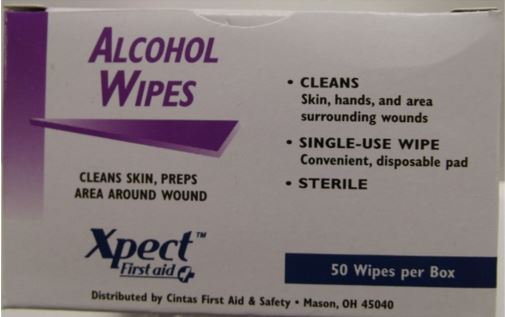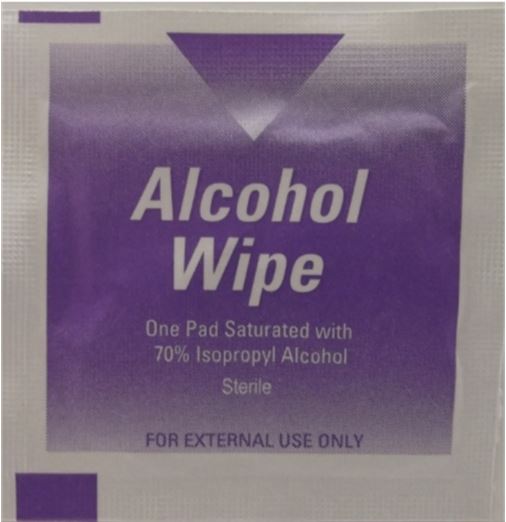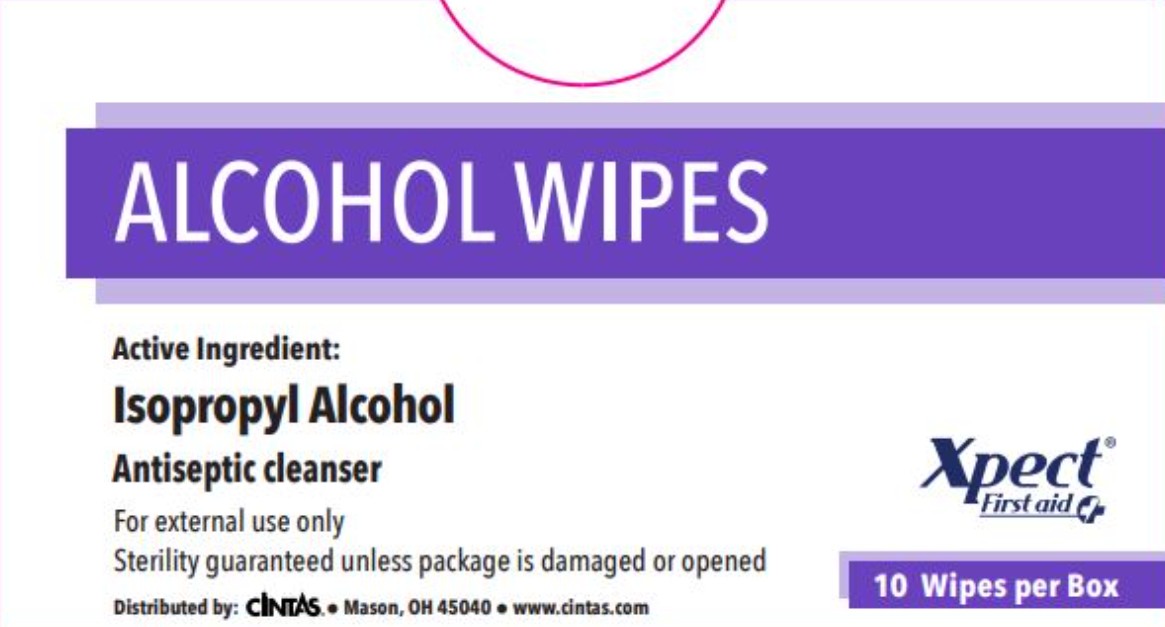 DRUG LABEL: Xpect Alcohol Wipes
NDC: 42961-226 | Form: SPONGE
Manufacturer: Cintas Corporation
Category: otc | Type: HUMAN OTC DRUG LABEL
Date: 20250929

ACTIVE INGREDIENTS: ISOPROPYL ALCOHOL .7 mL/.7 mL
INACTIVE INGREDIENTS: WATER

Xpect Alcohol Wipes

Active ingredients (in each towelette)

Isopropyl Alcohol 70%

Purpose

first aid antiseptic

Uses

first aid to help prevent infection in minor cuts, scrapes, and burns

Warnings

- For external use only
- Flammable, keep away from fire or flame

Do not use

- in the eyes or apply over large areas of the body
- longer than 1 week unless directed by a doctor

Ask a doctor before use if you have

- deep or puncture wounds
- animal bites
- serious burns

Stop use and ask a doctor if

condition persists or gets worse

Keep out of reach of children. If swallowed, get medical help or contact a Poison Control Center right away.

Directions

- clean the affected area
- apply a small amount of this product on the area 1-3 times daily
- may be covered with a sterile bandage. If bandaged, let dry first.

Other information

- do not use if packet is torn, cut or opened
- store at room temperature

Inactive ingredients

deionized water

Questions?

1-877-973-2811 www.cintas.com

Principal Display - Box 10 count

ALCOHOL WIPES

Active Ingredient:

Isopropyl Alcohol

Antiseptic cleanser

For external use only

Sterility guaranteed unless package is damaged or opened

Distributed by: Cintas® • Mason, OH 45040 • www.cintas.com

Xpect® First aid

10 Wipes per Box

Principal Display - Box 50 count

ALCOHOL WIPES

CLEANS SKIN, PREPS AREA AROUND WOUND

- CLEANS

Skin, hands, and area surrounding wounds

- SINGLE-USE WIPE

Convenient, disposible pad

- STERILE

50 Wipes per Box

Xpect First Aid